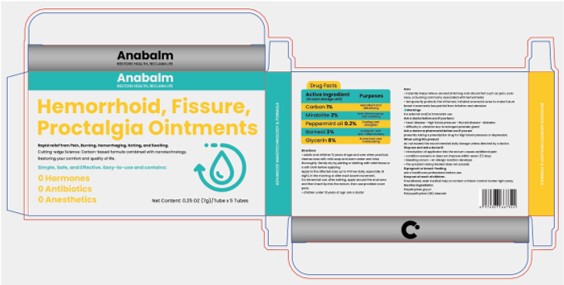 DRUG LABEL: Hemorrhoid, Fissure, Proctalgia Ointments
NDC: 84533-003 | Form: SALVE
Manufacturer: WU XI ZHONG ZHI WEI NA TECHNOLOGY CO., Ltd.
Category: otc | Type: HUMAN OTC DRUG LABEL
Date: 20260114

ACTIVE INGREDIENTS: SODIUM SULFATE 2 g/100 g; BORNEOL 3 g/100 g; ACTIVATED CHARCOAL 1 g/100 g; PEPPERMINT OIL 0.2 g/100 g; GLYCERIN 8 g/100 g
INACTIVE INGREDIENTS: PEG-23 STEARATE; POLYETHYLENE GLYCOL, UNSPECIFIED

84533-003 Hemorrhoid, Fissure, Proctalgia Ointment

ACTIVE INGREDIENT

Carbon 1%
Mirabilite 2%
Peppermint oil 0.2%
Borneol 3%
Glycerin 8%

PURPOSE

Adsorbent and detoxifying
Anti-infmmatoty and soothing
cooling and analgesic
Analgesic and anti-infiommatoey
Humectant and moistueizing

Keep out of reaah of children.
if swallowed, seek medical help or contact a poison control center right away.

INDICATIONS AND USAGE

instantly heips relieve anorectai itching and discomfort such as pain, sore-ness or burning commonlyassociated with hemorhoids.
tomporarily protects the inflamed, irritated anorectal area to make futurebowei mowements less painfut from irritation and abrasion.

WARNINGS

For eoternat and/or intrarectal use.

DOSAGE AND ADMINISTRATION

.aduits and chlkdren 12 years of oage and oer when practical,cleanse area with mild soap and warm water and rinsethorcughiy, Gently dry by patting or blotting with tollet tissue ora sodt cloth before applying.Apply to the atfected area up to 4 times daily, cspecially atnight, in the moming or after each bowei movement.For intrarectaluse: after watting, apply around the anad creaand then insert tip into tho reatum, then use provided oowerpads.
. children under 12 yoars cf age ask a doctor

INACTIVE INGREDIENT

Polyethylene Glycol
Polyoxyethylene (40) Stearate